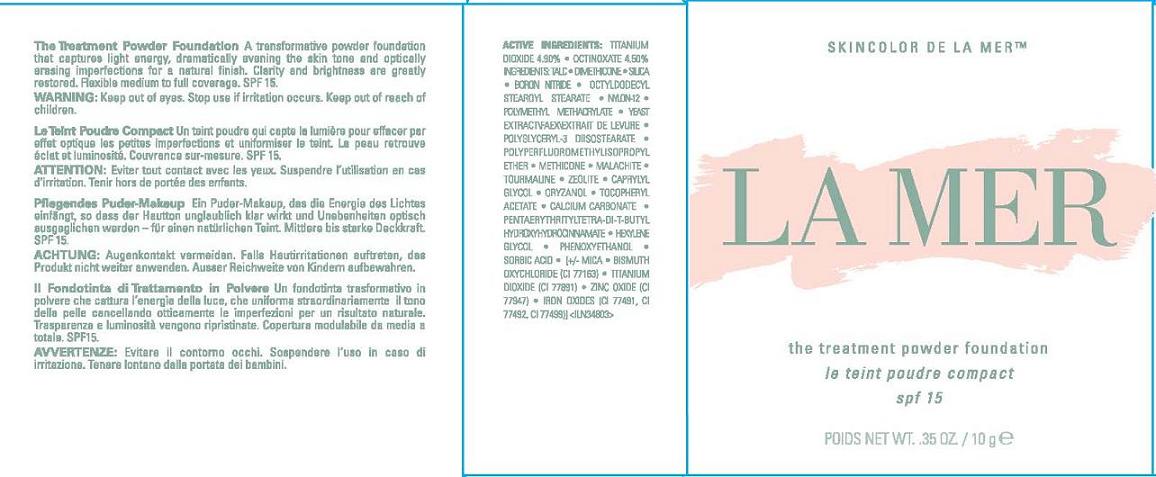 DRUG LABEL: THE TREATMENT POWDER FOUNDATION
NDC: 65966-111 | Form: POWDER
Manufacturer: MAX HUBER RESEARCH LAB INC
Category: otc | Type: HUMAN OTC DRUG LABEL
Date: 20110714

ACTIVE INGREDIENTS: TITANIUM DIOXIDE 4.9 g/100 g; OCTINOXATE 4.5 g/100 g
INACTIVE INGREDIENTS: TALC; DIMETHICONE; SILICON DIOXIDE; BORON NITRIDE; OCTYLDODECYL STEAROYL STEARATE; YEAST; CUPRIC CARBONATE; CAPRYLYL GLYCOL; GAMMA ORYZANOL; ALPHA-TOCOPHEROL ACETATE; CALCIUM CARBONATE; PENTAERYTHRITOL TETRAKIS(3-(3,5-DI-TERT-BUTYL-4-HYDROXYPHENYL)PROPIONATE); HEXYLENE GLYCOL; PHENOXYETHANOL; SORBIC ACID; BISMUTH OXYCHLORIDE; ZINC OXIDE; FERROSOFERRIC OXIDE; FERRIC OXIDE YELLOW; FERRIC OXIDE RED

ACTIVE INGREDIENT

ACTIVE INGREDIENTS: TITANIUM DIOXIDE, 4.9% [] OCTINOXATE 4.5%

INACTIVE INGREDIENT

INACTIVE INGREDIENTS: TALC [] DIMETHICONE [] SILICA [] BORON NITRIDE [] OCTYLDODECYL STEAROYL STEARATE [] NYLON-12 [] POLYMETHYL METHACRYLATE [] YEAST EXTRACT\FAEX\EXTRAIT DE LEVURE [] POLYGLYCERYL-3 DIISOSTEARATE [] POLYPERFLUOROMETHYLISOPROPYL ETHER [] METHICONE [] MALACHITE [] TOURMALINE [] ZEOLITE [] CAPRYLYL GLYCOL [] ORYZANOL [] TOCOPHERYL ACETATE [] CALCIUM CARBONATE [] PENTAERYTHRITYL TETRA-DI-T-BUTYL HYDROXYHYDROCINNAMATE [] HEXYLENE GLYCOL [] PHENOXYETHANOL [] SORBIC ACID [] [+/- MICA [] BISMUTH OXYCHLORIDE (CI 77163) [] TITANIUM DIOXIDE (CI 77891) [] ZINC OXIDE (CI 77947) [] IRON OXIDES (CI 77491, CI 77492, CI 77499)]

WARNINGS

WARNING: KEEP OUT OF EYES. STOP USE IF IRRITATION OCCURS. KEEP OUT OF REACH OF CHILDREN.

PACKAGE LABEL

PRINCIPAL DISPLAY PANEL:

skin color de la mer

LA MER

the treatment powder foundation

spf 15

nt wt. 0.35 oz./10 g

MAX HUBER RESEARCH LABS INC DISTR.

NEW YORK, NY 10022